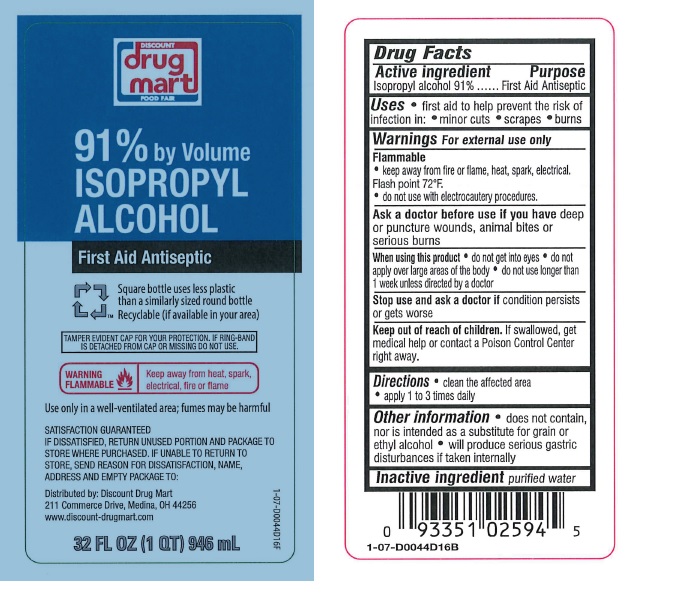 DRUG LABEL: Isopropyl Alcohol
NDC: 53943-091 | Form: LIQUID
Manufacturer: Discount Drug Mart
Category: otc | Type: HUMAN OTC DRUG LABEL
Date: 20260112

ACTIVE INGREDIENTS: ISOPROPYL ALCOHOL 91 mL/100 mL
INACTIVE INGREDIENTS: WATER

Isopropyl Alcohol 91%

Drug Facts

Active ingredient

Isopropyl alcohol 91%

Purpose

First Aid Antiseptic

Uses

- first aid to help prevent the risk of infection in:
  - minor cuts
  - scrapes
  - burns

Warnings

For external use only

Flammable

- keep away from fire or flame, heat, spark, electrical. Flash point 72°F.

Ask a doctor before use if you havedeep or puncture wounds, animal bites or serious burns

When using this product

- do not get into eyes
- do not apply over large areas of the body
- do not use longer than 1 week unless directed by a doctor

Stop use and ask a doctor ifcondition persists or gets worse

Keep out of reach of children.If swallowed, get medical help or contact a Poison Control Center right away.

Directions

- clean the affected area
- apply 1 to 3 times daily

Other information

- does not contain, nor is intended as a substitute for grain or ethyl alcohol
- will produce serious gastric disturbances if taken internally

Inactive ingredient

purified water

PRINCIPAL DISPLAY PANEL

Discount

drug

mart

Food FAIR

91% by Volume

ISOPROPYL ALCOHOL

First Aid Antiseptic

Square bottle uses less plastic than a similarly sized round bottle

Recyclable (If available in your area)

TAMPER EVIDENT CAP FOR YOUR PROTECTION.

IF RING-BAND IS DETACHED FROM CAP OR MISSING DO NOT USE.

Warning

Flammable

Keep away from heat, spark, electrical, fire or flame

Use only in a well-ventillated area; fumes may be harmful

SATISFACTION GUARANTEED.

IF DISSATISFIED. RETURN UNUSED PORTION AND PACKAGE TO

STORE WHERE PURCHASED. IF UNABLE TO RETURN TO STORE,

SEND REASON FOR DISSATISFACTION, NAME, ADDRESS AND EMPTY PACKAGE TO:

Distributed by: Discount Drug Mart

211 Commerce Drive, Medina, OH 44256

www.discount-drugmart.com

32 FL. OZ. (946 mL)